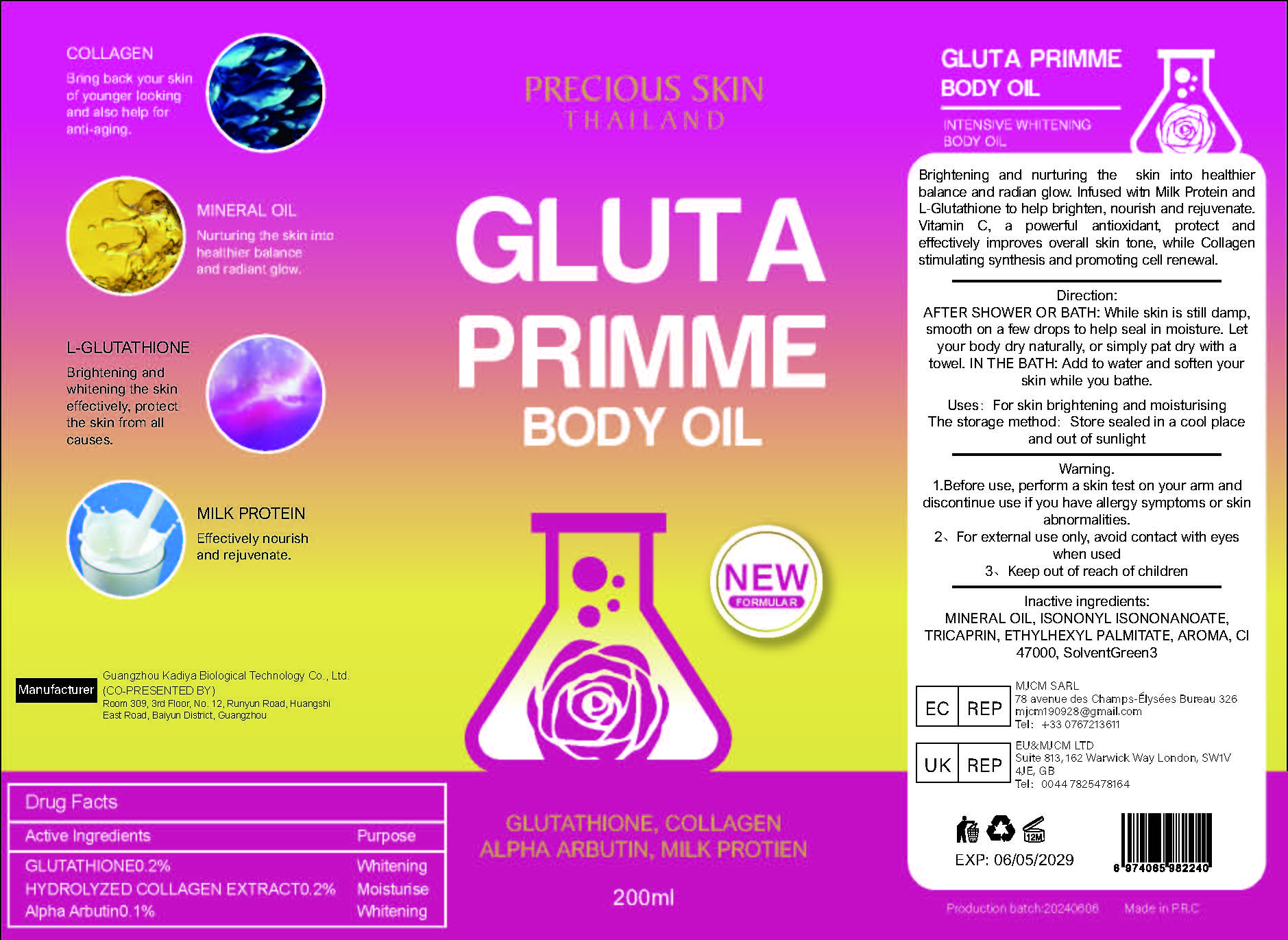 DRUG LABEL: GLUTA PRIMME body oil
NDC: 84423-009 | Form: OIL
Manufacturer: Guangzhou Kadiya Biotechnology Co. Ltd.
Category: otc | Type: HUMAN OTC DRUG LABEL
Date: 20240628

ACTIVE INGREDIENTS: ALPHA-ARBUTIN 0.2 mg/200 mg; GLUTATHIONE 0.4 mg/200 mg
INACTIVE INGREDIENTS: MINERAL OIL; D&C YELLOW NO. 11; TRICAPRIN; ISONONYL ISONONANOATE; ETHYLHEXYL PALMITATE

Active Ingredients

GLUTATHIONE0.2%
Alpha Arbutin0.1%

PURPOSE

For skin brightening and moisturising

Warning

1.Before use, perform a skin test on your arm and discontinue use if you have allergy symptoms or skin abnormalities.
2、For external use only, avoid contact with eyes when used
3、Keep out of reach of children

INACTIVE INGREDIENT

MINERAL OIL、ISONONYL ISONONANOATE、TRICAPRIN、ETHYLHEXYL PALMITATE、CI 47000

USAGE

For skin brightening and moisturising

Dosage

AFTER SHOWER OR BATH: While skin is still damp, smooth on a few drops to help seal in moisture. Let your body dry naturally, or simply pat dry with a towel. IN THE BATH: Add to water and soften your skin while you bathe.

Warning

Out of reach of children

Drug Facts
Active Ingredients
GLUTATHIONE0.2%
Alpha Arbutin0.1%
Uses：
For skin brightening and moisturising
The storage method：
Store sealed in a cool place and out of sunlight
Warning.
1.Before use, perform a skin test on your arm and discontinue use if you have allergy symptoms or skin abnormalities.
2、For external use only, avoid contact with eyes when used
3、Keep out of reach of children
Inactive ingredients：
MINERAL OIL、ISONONYL ISONONANOATE、TRICAPRIN、ETHYLHEXYL PALMITATE、CI 47000